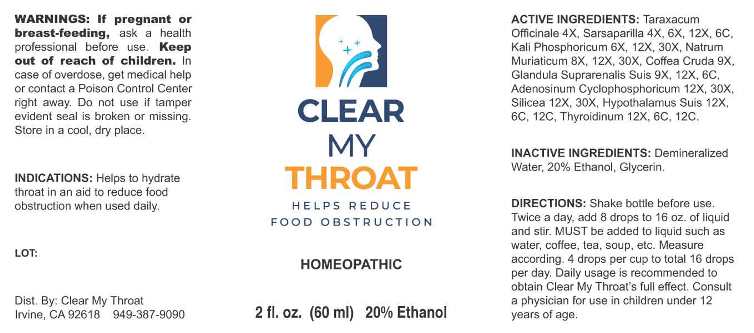 DRUG LABEL: Clear My Throat
NDC: 78892-0001 | Form: LIQUID
Manufacturer: Shirley Dieu dba Clear My Throat
Category: homeopathic | Type: HUMAN OTC DRUG LABEL
Date: 20240122

ACTIVE INGREDIENTS: TARAXACUM OFFICINALE 4 [hp_X]/1 mL; SMILAX ORNATA ROOT 4 [hp_X]/1 mL; DIBASIC POTASSIUM PHOSPHATE 6 [hp_X]/1 mL; SODIUM CHLORIDE 8 [hp_X]/1 mL; ARABICA COFFEE BEAN 9 [hp_X]/1 mL; SUS SCROFA ADRENAL GLAND 9 [hp_X]/1 mL; ADENOSINE CYCLIC PHOSPHATE 12 [hp_X]/1 mL; SILICON DIOXIDE 12 [hp_X]/1 mL; SUS SCROFA HYPOTHALAMUS 12 [hp_X]/1 mL; THYROID, BOVINE 12 [hp_X]/1 mL
INACTIVE INGREDIENTS: WATER; GLYCERIN; ALCOHOL

Drug Facts:

ACTIVE INGREDIENTS:

Taraxacum Officinale 4X, Sarsaparilla (Smilax Regelii) 4X, 6X, 12X, 6C, Kali Phosphoricum 6X, 12X, 30X, Natrum Muriaticum 8X, 12X, 30X, Coffea Cruda 9X, Glandula Suprarenalis Suis 9X, 12X, 6C, Adenosinum Cyclophosphoricum 12X, 30X, Silicea 12X, 30X, Hypothalamus Suis 12X, 6C, 12C, Thyroidinum (Bovine) 12X, 6C, 12C.

INDICATIONS:

Helps to hydrate throat in an aid to reduce food obstruction when used daily.

WARNINGS:

If pregnant or breast-feeding, ask a health professional before use.

Keep out of reach of children. In case of overdose, get medical help or contact a Poison Control Center right away.

Do not use if tamper evident seal is broken or missing. Store in a cool, dry place.

Keep out of reach of children. In case of overdose, get medical help or contact a Poison Control Center right away.

DIRECTIONS:

Shake bottle before use. Twice a day, add 8 drips to 16 oz. of liquid and stir. MUST be added to liquid such as water, coffee, tea, soup, etc. Measure according. 4 drops per cup to total 16 drops per day. Daily usage is recommended to obtain Clear My Throat's full effect. Consult a physician for use in children under 12 years of age.

INDICATIONS:

Helps to hydrate throat in an aid to reduce food obstruction when used daily.

INACTIVE INGREDIENTS:

Demineralized Water, 20% Ethanol, Glycerin.

QUESTIONS:

Dist. By: Clear My Throat

Irvine, Ca 92618 949-387-9090

PACKAGE LABEL DISPLAY:

CLEAR

MY

THROAT

HELPS REDUCE

FOOD OBSTRUCTION

HOMEOPATHIC

2 fl. oz. (60 ml)